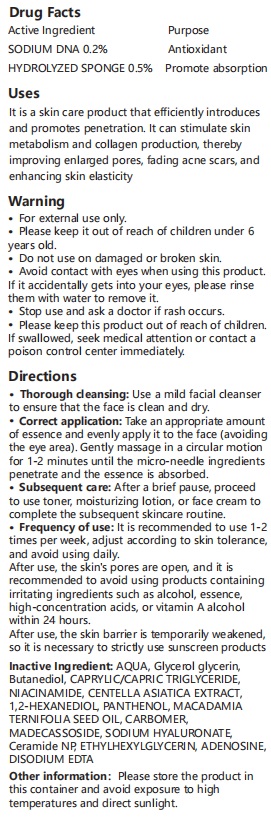 DRUG LABEL: BioMicroneedle PDRN Cream
NDC: 87092-002 | Form: CREAM
Manufacturer: Guangzhou Shengyanghui Industrial Trading Co., Ltd
Category: otc | Type: HUMAN OTC DRUG LABEL
Date: 20260121

ACTIVE INGREDIENTS: SILICON DIOXIDE 0.5 g/100 g
INACTIVE INGREDIENTS: CARBOMER 0.2 g/100 g; SODIUM HYALURONATE 0.1 g/100 g; 1,2-BUTANEDIOL 5 g/100 g; 1,2-HEXANEDIOL 2 g/100 g; PANTHENOL 1 g/100 g; CERAMIDE NP 0.05 g/100 g; MACADAMIA TERNIFOLIA SEED OIL 1 g/100 g; NIACINAMIDE 2 g/100 g; AQUA 74.74 g/100 g; CENTELLA ASIATICA WHOLE 2 g/100 g; CAPRYLIC/CAPRIC TRIGLYCERIDE 3 g/100 g; MADECASSOSIDE 0.1 g/100 g; SODIUM LAURYL SARCOSINATE 0.2 g/100 g; EDETATE DISODIUM 0.02 g/100 g; ADENOSINE 0.04 g/100 g; GLYCERIN 8 g/100 g; ETHYLHEXYLGLYCERIN 0.05 g/100 g

ACTIVE INGREDIENT

SODIUM DNA 0.2%(0.2ml/100ml)

HYDROLYZED SPONGE 0.5%(0.5ml/100ml)

PURPOSE

Antioxidant
Promote absorption

KEEP OUT OF REACH OF CHILDREN

Please keep it out of reach of children under 6
years old.

WARNINGS

. For external use only.
Please keep it out of reach of children under 6
years old.
.
Do not use on damaged or broken skin.
.
Avoid contact with eyes when using this product.
If it accidentally gets into your eyes, please rinse
them with water to remove it.
.
Stop use and ask a doctor if rash occurs.
. Please keep this product out of reach of children.
If swallowed, seek medical attention or contact a
poison control center immediately

INDICATIONS AND USAGE

It is a skin care product that efficiently introduces
and promotes penetration. It can stimulate skin
metabolism and collagen production, thereby
improving enlarged pores, fading acne scars, and
enhancing skin elasticity

WHEN USING

. Thorough cleansing: Use a mild facial cleanser
to ensure that the face is clean and dry.
.
Correct application: Take an appropriate amount
of essence and evenly apply it to the face (avoiding
the eye area). Gently massage in a circular motion
for 1-2 minutes until the micro-needle ingredients
penetrate and the essence is absorbed.
. Subsequent care: After a brief pause, proceed
to use toner, moisturizing lotion, or face cream to
complete the subsequent skincare routine.
. Frequency of use: It is recommended to use 1-2
times per week, adjust according to skin tolerance,
and avoid using daily.
After use, the skin's pores are open, and it is
recommended to avoid using products containing
irritating ingredients such as alcohol, essence,
high-concentration acids, or vitamin A alcohol
within 24 hours.
After use, the skin barrier is temporarily weakened,
so it is necessary to strictly use sunscreen products

Inactive Ingredient: AQUA, Glycerol glycerin,
Butanediol, CAPRYLIC/CAPRIC TRIGLYCERIDE,
NIACINAMIDE, CENTELLA ASIATICA EXTRACT,
1,2-HEXANEDIOL, PANTHENOL, MACADAMIA
TERNIFOLIA SEED OIL, CARBOMER,
MADECASSOSIDE, SODIUM HYALURONATE,
Ceramide NP, ETHYLHEXYLGLYCERIN, ADENOSINE,
DISODIUM EDTA

DOSAGE AND ADMINISTRATION

. Frequency of use: It is recommended to use 1-2
times per week, adjust according to skin tolerance,
and avoid using daily.